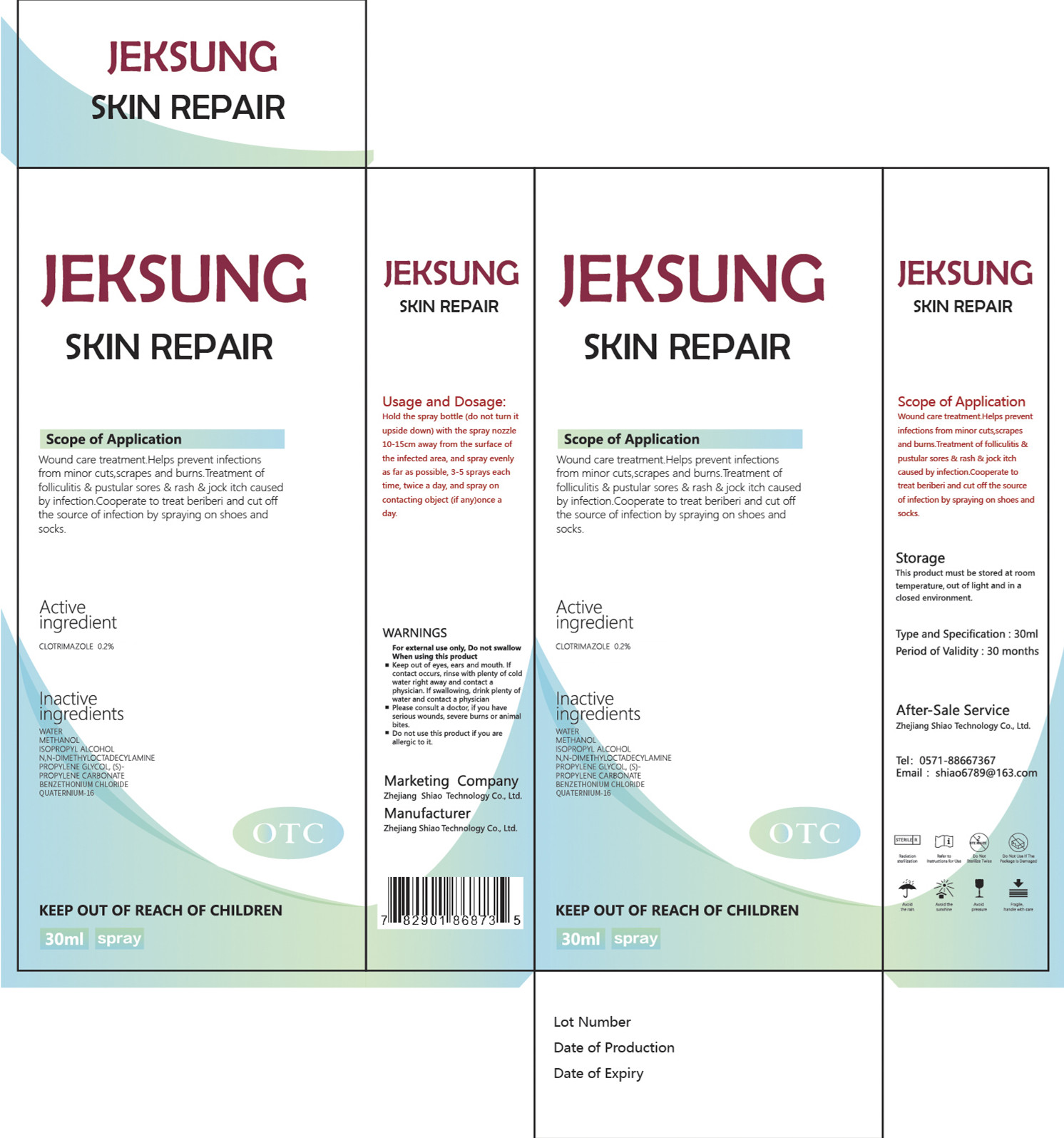 DRUG LABEL: SKIN REPAIR
NDC: 55451-010 | Form: SPRAY
Manufacturer: Zhejiang Shiao Technology Co., Ltd.
Category: otc | Type: HUMAN OTC DRUG LABEL
Date: 20200427

ACTIVE INGREDIENTS: CLOTRIMAZOLE 0.06 mg/30 mL
INACTIVE INGREDIENTS: BENZETHONIUM CHLORIDE; QUATERNIUM-16; WATER; PROPYLENE CARBONATE; METHYL ALCOHOL; ISOPROPYL ALCOHOL; DYMANTHINE; PROPYLENE GLYCOL, (S)-

DOSAGE AND ADMINISTRATION

30ML, 3-5 sprays each time, twice a day

WARNINGS

For external use only, Do not swallow When using this product
Keep out of eyes, ears, and mouth. If contact occurs, rinse with plenty of cold water right away and contact a physician. If swallowing, drink plenty of water and contact a physician
Please consult a doctor, if you have serious wounds, severe burns or animal bites.
Do not use this product if you are allergic to it.

INACTIVE INGREDIENT

WATER
METHANOL
ISOPROPYL ALCOHOL
N,N-DIMETHYLOCTADECYL AMINE
PROPYLENE GLYCOL, (S)-
PROPYLENE CARBONATE

BENZETHONIUM CHLORIDE

QUATERNIUM-16

ACTIVE INGREDIENT

CLOTRIMAZOLE

INDICATIONS AND USAGE

Hold the spray bottle (do not turn it upside down) withthe spray nozzle 10- 15cm away from the surface of the infectedarea, andspray evenly as far as possible, 3-5 sprays each time, twice a day, andspray on contacting object (if any)once a day. Each dose can be increased or decreased according to the actual situation of the patient. In severe cases, 10-15 sprays are recommended until the acute inflammation or major symptoms disappear.

KEEP OUT OF REACH OF CHILDREN

PURPOSE

This product can be used for anti-inflammatory debridement of wounds, and treatment of hair folliculitis, pustule sores, and jock itches caused by bacterial infection. It can also cooperate to treat beriberi, and cut off the source of infection by spraying on shoes and socks.